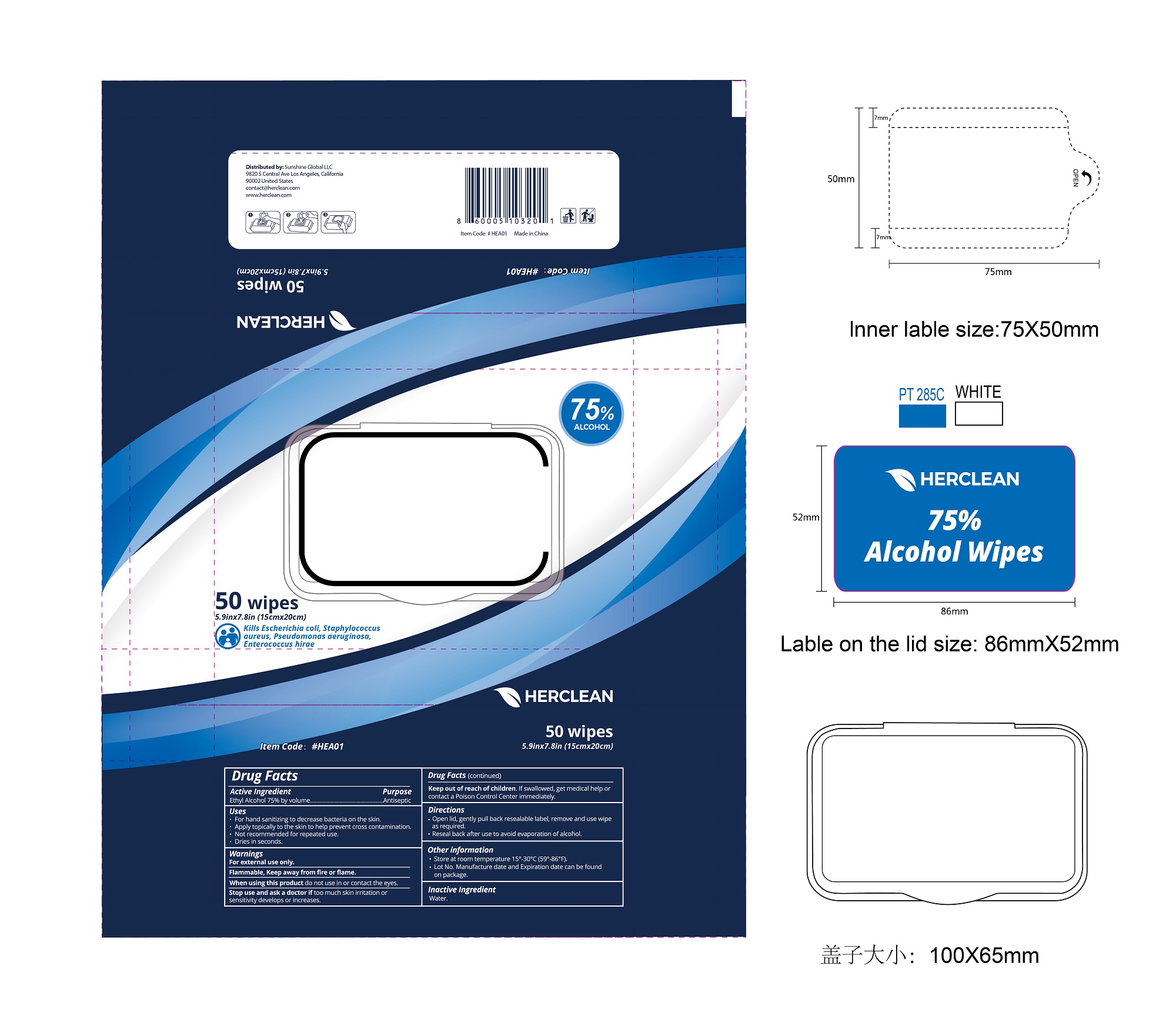 DRUG LABEL: Herclean Alcohol wipes
NDC: 75109-515 | Form: CLOTH
Manufacturer: Kangna (Zhejiang) Medical Supplies Co., Ltd.
Category: otc | Type: HUMAN OTC DRUG LABEL
Date: 20220114

ACTIVE INGREDIENTS: ALCOHOL 75 mL/100 mL
INACTIVE INGREDIENTS: WATER

75109-515 Herclean Alcohol wipes 75% Alcohol

Active Ingredient

Alcohol 75% by volume

Purpose

Antiseptic

USE

Uses■for hand sanitizing to decrease bacteria on the skin■apply
topically to the skin to help prevent cross contamination■not recommended
for repeated use■dries in seconds

Warning

For external use only. Flammable, keep away from fire or flame.
When using this product keep out of eyes, ears, and mouth. In case of eye contact, flush thoroughly with water.
Stop use and ask doctor if irritation or rash occurs. These may be signs of a serious condition.

Keep out of reach of children. If swallowed, get medical help or contact a Posion Control Center right away.

Directions

.Open lid, gently pull back resealable label, remove and use wipe as required.
Reseal back after use to avoid evaporation of alcohol.
Other information
.Store at room temperature 15°-30°C (59°-86°F).
. Lot No. Manufacture date and Expiration date can be found on package.

Inactive ingredients

Water